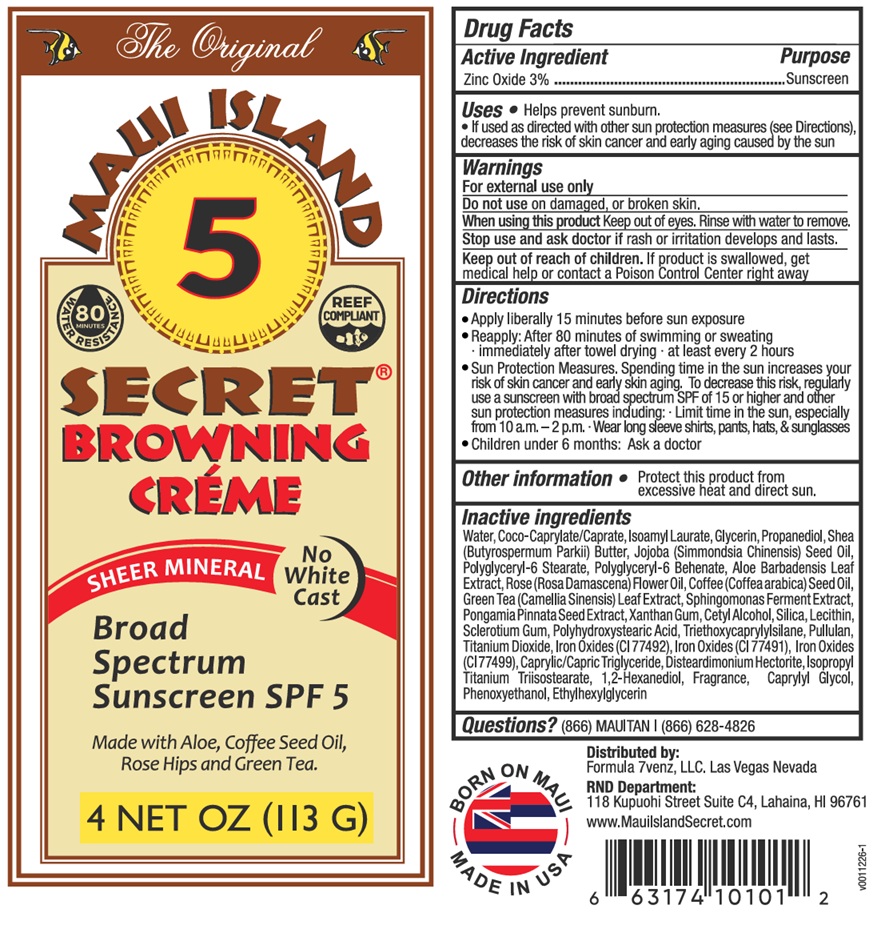 DRUG LABEL: MAUI ISLAND SECRET BROWNING CREME Broad Spectrum Sunscreen SPF 5
NDC: 82086-003 | Form: CREAM
Manufacturer: Formula 7venz L.L.C.
Category: otc | Type: HUMAN OTC DRUG LABEL
Date: 20251231

ACTIVE INGREDIENTS: ZINC OXIDE 3 g/100 g
INACTIVE INGREDIENTS: WATER; COCOYL CAPRYLOCAPRATE; ISOAMYL LAURATE; GLYCERIN; PROPANEDIOL; SHEA BUTTER; JOJOBA OIL; POLYGLYCERYL-6 STEARATE; POLYGLYCERYL-6 BEHENATE; ALOE VERA LEAF; ROSA X DAMASCENA FLOWER OIL; ARABICA COFFEE OIL; GREEN TEA LEAF; FERMENT COMPLEX 6/PF; PONGAMIA PINNATA SEED; XANTHAN GUM; CETYL ALCOHOL; SILICON DIOXIDE; SOYBEAN LECITHIN; BETASIZOFIRAN; POLYHYDROXYSTEARIC ACID (2300 MW); TRIETHOXYCAPRYLYLSILANE; PULLULAN; TITANIUM DIOXIDE; FERRIC OXIDE YELLOW; FERRIC OXIDE RED; FERROSOFERRIC OXIDE; MEDIUM-CHAIN TRIGLYCERIDES; DISTEARDIMONIUM HECTORITE; ISOPROPYL TITANIUM TRIISOSTEARATE; 1,2-HEXANEDIOL; CAPRYLYL GLYCOL; PHENOXYETHANOL; ETHYLHEXYLGLYCERIN

MAUI ISLAND SECRET® BROWNING CRÉME Broad Spectrum Sunscreen SPF 5

Active Ingredient

Zinc Oxide 3%

Purpose

Sunscreen

Uses

• Helps prevent sunburn.
• If used as directed with other sun protection measures (see Directions), decreases the risk of skin cancer and early aging caused by the sun.

Warnings

For external use only
Do not use on damaged, or broken skin.
When using this product Keep out of eyes. Rinse with water to remove.
Stop use and ask doctor if rash or irritation develops or lasts.

Keep out of reach of children. If product is swallowed, get medical help or contact a Poison Control Center right away.

Directions

• Apply liberally 15 minutes before sun exposure
• Reapply: After 80 minutes of swimming or sweating
· immediately after towel drying · at least every 2 hours
• Sun Protection Measures. Spending time in the sun increases your risk of skin cancer and early skin aging. To decrease this risk, regularly use
a sunscreen with broad spectrum SPF of 15 or higher and other sun protection measures including: · Limit time in the sun, especially from 10
a.m.-2 p.m. · Wear long sleeve shirts, pants, hats, & sunglasses
• Children under 6 months: Ask a doctor

Other information

• Protect this product from excessive heat and direct sun.

Inactive ingredients

Water, Coco-Caprylate/Caprate, Isoamyl Laurate, Glycerin, Propanediol, Shea (Butyrospermum Parkii) Butter, Jojoba (Simmondsia Chinensis) Seed Oil, Polyglyceryl-6 Stearate, Polyglyceryl-6 Behenate, Aloe Barbadensis Leaf Extract, Rose (Rosa Damascena) Flower Oil, Coffee (Coffea Arabica) Seed Oil, Green Tea (Camellia Sinensis) Leaf Extract, Sphingomonas Ferment Extract, Pongamia Pinnata Seed Extract, Xanthan Gum, Cetyl Alcohol, Silica, Lecithin, Sclerotium Gum, Polyhydroxystearic Acid, Triethoxycaprylylsilane, Pullulan, Titanium Dioxide, Iron Oxides (Cl 77492), Iron Oxides (Cl 77491), Iron Oxides (Cl 77499), Caprylic/Capric Triglyceride, Disteardimonium Hectorite, Isopropyl Titanium Triisostearate, 1,2-Hexanediol, Fragrance, Caprylyl Glycol, Phenoxyethanol, Ethylhexylglycerin

Questions?

(866) MAUITAN | (866) 628-4826

The Original

80 MINUTES WATER RESISTANCE

REEF COMPLIANT

SHEER MINERAL NO WHITE CAST

Made with Aloe, Coffee Seed Oil, Rose Hips and Green Tea.

Distributed by:
Formula 7venz, LLC. Las Vegas Nevada

RND Department:
118 Kupuohi Street Suite C4, Lahaina, HI 96761

www.MauiIslandSecret.com

BORN ON MAUI
MADE IN USA